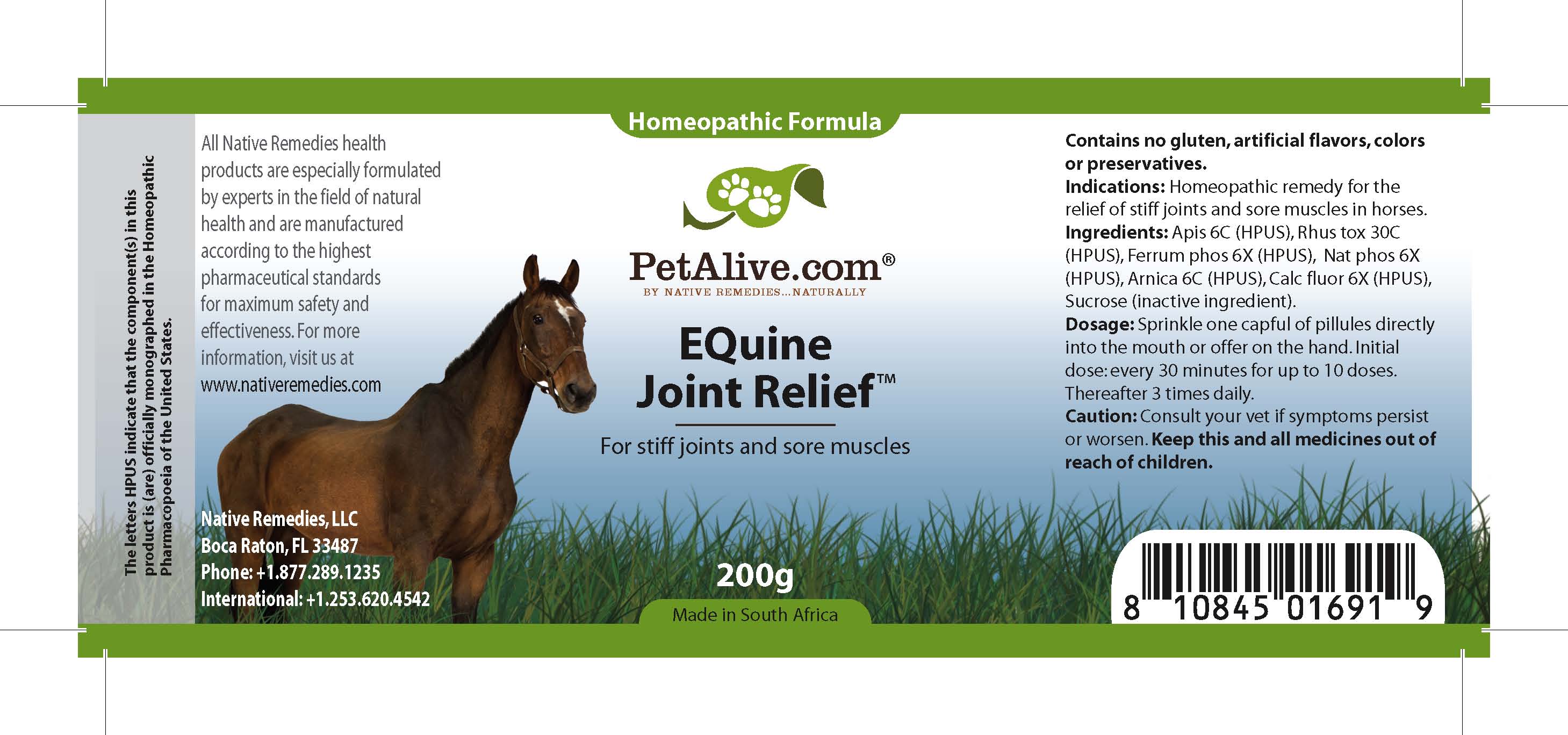 DRUG LABEL: Equine Joint Relief
NDC: 68647-187 | Form: GRANULE
Manufacturer: Feelgood Health
Category: homeopathic | Type: OTC ANIMAL DRUG LABEL
Date: 20100923

ACTIVE INGREDIENTS: APIS MELLIFERA 6 [hp_C]/33.3 mg; TOXICODENDRON PUBESCENS LEAF 30 [hp_C]/33.3 mg; FERRUM PHOSPHORICUM 6 [hp_X]/33.3 mg; SODIUM PHOSPHATE, DIBASIC ANHYDROUS 6 [hp_X]/33.3 mg; ARNICA MONTANA 6 [hp_C]/33.3 mg; CALCIUM FLUORIDE 6 [hp_X]/33.3 mg
INACTIVE INGREDIENTS: SUCROSE

EQUINE JOINT RELIEF

PURPOSE

For stiff joints and sore muscles

INDICATIONS AND USAGE

Indications: Homeopathic remedy for the relief of stiff joints and sore muscles in horses.

DOSAGE AND ADMINISTRATION

Dosage: Sprinkle 1 capful of pilules directly into the mouth or offer on the hand. Initial dose: every 30 minutes for up to 10 doses. Thereafter, 3 times daily.

GENERAL PRECAUTIONS

Caution: Consult your vet if symptoms persist or worsen. Keep this and all medicines out of reach of children.

ACTIVE INGREDIENT

Ingredients: Apis (6C) (HPUS), Rhus tox (30C) (HPUS), Ferrum phos (6X) (HPUS), Nat phos (6X) (HPUS), Arnica (6C) (HPUS), Calc fluor (6X) (HPUS)

Sucrose (inactive ingredient).

WARNINGS

Contains no gluten, artificial flavors, colors or preservatives.

PATIENT COUNSELING INFORMATION

All Native Remedies health products are especially formulated by experts in the field of natural health and are manufactured according to the highest pharmaceutical standards for maximum safety and effectiveness. For more information, visit us at www.petalive.com

Distributed by

Native Remedies, LLC

6531 Park of Commerce Blvd.

Suite 160

Boca Raton, FL 33487

Phone: 1.877.289.1235

International: + 1.561.999.8857

The letters HPUS indicate that the component(s) in this product is (are) officially monographed in the Homeopathic Pharmacopoeia of the United States.

KEEP OUT OF REACH OF CHILDREN

Keep this and all medicines out of reach of children.